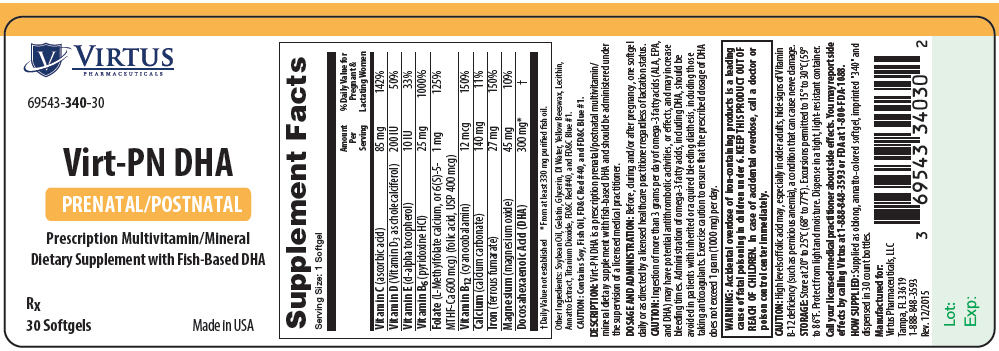 DRUG LABEL: Virt-PN DHA
NDC: 69543-340 | Form: CAPSULE
Manufacturer: Virtus Pharmaceuticals
Category: other | Type: DIETARY SUPPLEMENT
Date: 20160308

ACTIVE INGREDIENTS: ASCORBIC ACID 85 mg/1 1; CHOLECALCIFEROL 200 [iU]/1 1; .ALPHA.-TOCOPHEROL, D- 10 [iU]/1 1; PYRIDOXINE HYDROCHLORIDE 25 mg/1 1; LEVOMEFOLATE CALCIUM 600 ug/1 1; FOLIC ACID 400 ug/1 1; CYANOCOBALAMIN 12 ug/1 1; CALCIUM CARBONATE 140 mg/1 1; FERROUS FUMARATE 27 mg/1 1; MAGNESIUM OXIDE 45 mg/1 1; DOCONEXENT 300 mg/1 1
INACTIVE INGREDIENTS: YELLOW WAX; SOYBEAN OIL; GELATIN; GLYCERIN; WATER; TITANIUM DIOXIDE; FD&C RED NO. 40; ANNATTO; FD&C BLUE NO. 1

Virt-PN DHA
PRENATAL/POSTNATAL

HEALTH CLAIM

Supplement Facts
Serving Size: 1 Softgel
 | Amount Per Serving | % Daily Value for Pregnant and Lactating Women
Vitamin C (ascorbic acid) | 85 mg | 142%
Vitamin D (Vitamin D3 as cholecalciferol) | 200 IU | 50%
Vitamin E (d-alpha tocopherol) | 10 IU | 33%
Vitamin B6 (pyridoxine HCl) | 25 mg | 1000%
Folate (L-Methylfolate calcium, or 6(S)-5-MTHF-Ca 600 mcg) (folic acid, USP 400 mcg) | 1 mg | 125%
Vitamin B12 (cyanocobalamin) | 12 mcg | 150%
Calcium (calcium carbonate) | 140 mg | 11%
Iron (ferrous fumarate) | 27 mg | 150%
Magnesium (magnesium oxide) | 45 mg | 10%
Docosahexaenoic Acid (DHA) | 300 mg [From at least 330 mg purified fish oil.] | [Daily Value not established]

Other Ingredients: Soybean Oil, Gelatin, Glycerin, DI Water, Yellow Beeswax, Lecithin, Annatto Extract, Titanium Dioxide, FD&C Red #40, and FD&C Blue #1.

CAUTION: Contains Soy, Fish Oil, FD&C Red #40, and FD&C Blue #1.

DESCRIPTION

Virt-PN DHA is a prescription prenatal/postnatal multivitamin/mineral dietary supplement with fish-based DHA and should be administered under the supervision of a licensed medical practitioner.

DOSAGE AND ADMINISTRATION

Before, during and/or after pregnancy, one softgel daily or as directed by a licensed healthcare practitioner regardless of lactation status.

CAUTION

Ingestion of more than 3 grams per day of omega-3 fatty acids (ALA, EPA, and DHA) may have potential antithrombotic activities, or effects, and may increase bleeding times. Administration of omega-3 fatty acids, including DHA, should be avoided in patients with inherited or acquired bleeding diathesis, including those taking anticoagulants. Exercise caution to ensure that the prescribed dosage of DHA does not exceed 1 gram (1000 mg) per day.

WARNINGS

WARNING: Accidental overdose of iron-containing products is a leading cause of fatal poisoning in children under 6. Keep this product out of reach of children. In case of accidental overdose, call a doctor or poison control center immediately.

CAUTION

High levels of folic acid may, especially in older adults, hide signs of Vitamin B-12 deficiency (such as pernicious anemia), a condition that can cause nerve damage.

SAFE HANDLING WARNING

Store at 20° to 25°C (68° to 77°F). Excursions permitted to 15° to 30°C (59° to 86°F. Protect from light and moisture. Dispense in a tight, light-resistant container. Notice: Contact with moisture may produce surface discoloration or erosion.

HEALTH CLAIM

Call your licensed medical practitioner about side effects. You may report side effects by calling Virtus at 1-888-848-3593 or FDA at 1-800-FDA-1088.

HOW SUPPLIED

Supplied as oblong, annatto-colored softgel, imprinted "340" and dispensed in 30 count bottles.

HEALTH CLAIM

Manufactured for:
Virtus Pharmaceuticals, LLC
Tampa, Florida 33619 1-888-848-3593

Rev. 12/2015

PRINCIPAL DISPLAY PANEL - 30 Softgel Bottle Label

VIRTUS
PHARMACEUTICALS

69543-340-30

Virt-PN DHA

PRENATAL/POSTNATAL

Prescription Multivitamin/Mineral
Dietary Supplement with Fish-Based DHA

Rx

30 Softgels
Made in USA